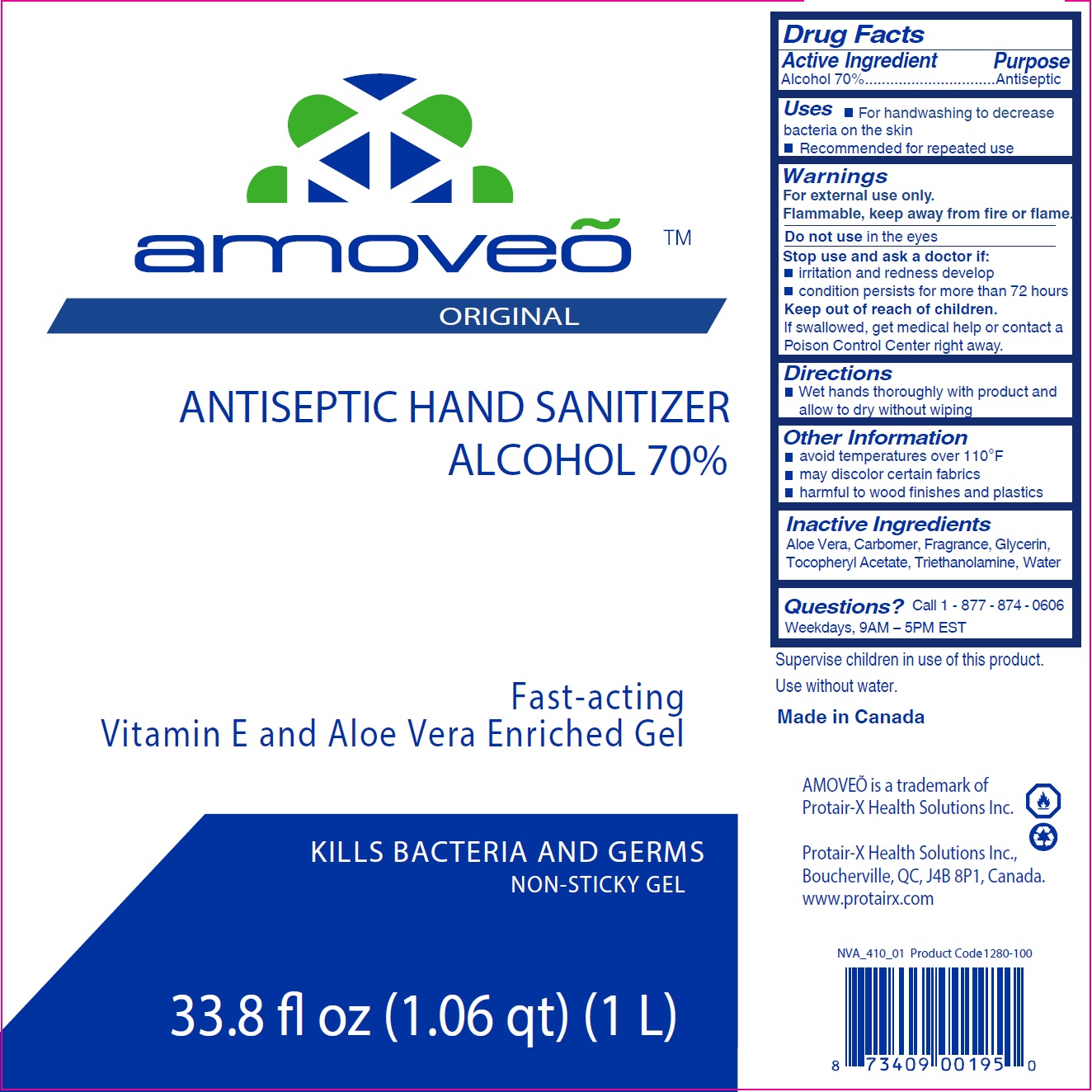 DRUG LABEL: Amoveo Original
NDC: 49955-701 | Form: GEL
Manufacturer: Protair-X Health Solutions Inc.
Category: otc | Type: HUMAN OTC DRUG LABEL
Date: 20170224

ACTIVE INGREDIENTS: ALCOHOL 700 mg/1 mL
INACTIVE INGREDIENTS: ALOE VERA LEAF; CARBOXYPOLYMETHYLENE; GLYCERIN; .ALPHA.-TOCOPHEROL ACETATE; TROLAMINE; WATER

Amoveo Original

Active Ingredient

Alcohol 80%

Purpose

Antiseptic

Uses

- For handwashing to decrease bacteria on the skin
- Recommended for repeated use

Warnings

For external use only.
Flammable, keep away from fire or flame.

Do not use

in the eyes

Stop use and ask a doctor if:

- irritation and redness develop
- condition persists for more than 72 hours

Keep out of reach of children.

If swallowed, get medical help or contact a Poison Control Center right away.

Directions

- Wet hands thoroughly with product and allow to dry without wiping

Other Information

- avoid temperatures over 110°F
- may discolor certain fabrics
- harmful to wood finishes and plastics

Inactive Ingredients

Aloe Vera, Carbomer, Fragrance, Glycerin, Tocopheryl Acetate, Triethanolamine, Water

Questions?

Call 1 - 877 - 874 - 0606 Weekdays, 9AM – 5PM EST